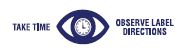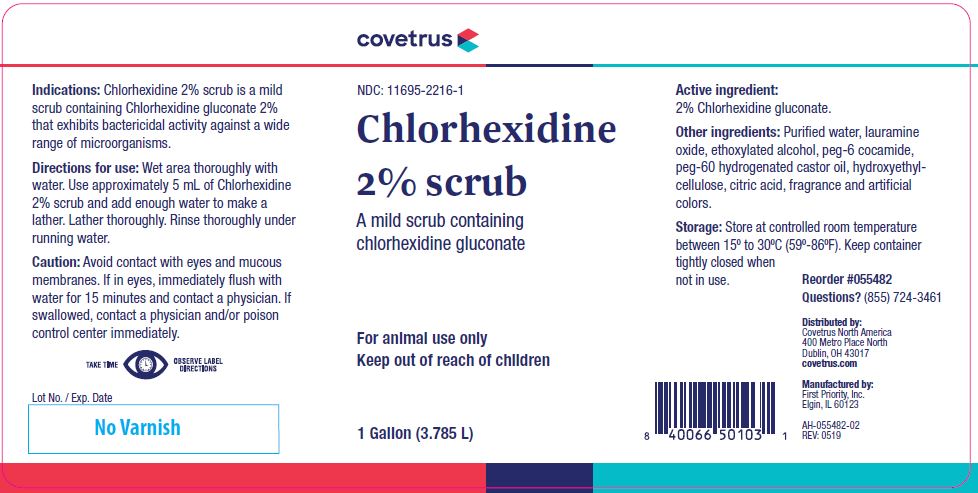 DRUG LABEL: Chlorhexidine Scrub
NDC: 11695-2216 | Form: LIQUID
Manufacturer: Butler Animal health Supply, LLC dba Covetrus North America
Category: animal | Type: OTC ANIMAL DRUG LABEL
Date: 20221111

ACTIVE INGREDIENTS: CHLORHEXIDINE GLUCONATE 100.9 g/1 L

Chlorhexidine 2% scrub

STATEMENT OF IDENTITY

A mild scrub containing chlorhexidine gluconate

KEEP OUT OF REACH OF CHILDREN

For animal use only
Keep out of reach of children

Indications:

Chlorhexidine 2% scrub is a mild scrub containing Chlorhexidine gluconate 2% that exhibits bactericidal activity against a wide range of microorganisms.

Directions for use:

Wet area thoroughly with water. Use approximately 5 mL of Chlorhexidine 2% scrub and add enough water to make a lather. Lather thoroughly. Rinse thoroughly under running water.

Caution:

Avoid contact with eyes and mucous membranes. If in eyes, immediately flush with water for 15 minutes and contact a physician. If swallowed, contact a physician and/or poison control center immediately.

Active ingredient:

2% Chlorhexidine gluconate.

Other ingredients:

Purified water, lauramine oxide, ethoxylated alcohol, peg-6 cocamide, peg-60 hydrogenated castor oil, hydroxyethylcellulose, citric acid, fragrance and artificial colors.

Storage:

Store at controlled room temperature between 15º to 30ºC (59º-86ºF). Keep container tightly closed when not in use.

HOW SUPPLIED

1 Gallon (3.785 L)

Questions? (855) 724-3461
Distributed by:
Covetrus North America
400 Metro Place North
Dublin, OH 43017
covetrus.com

Manufactured by:
First Priority, Inc.
Elgin, IL 60123

AH-055482-02
REV: 0519